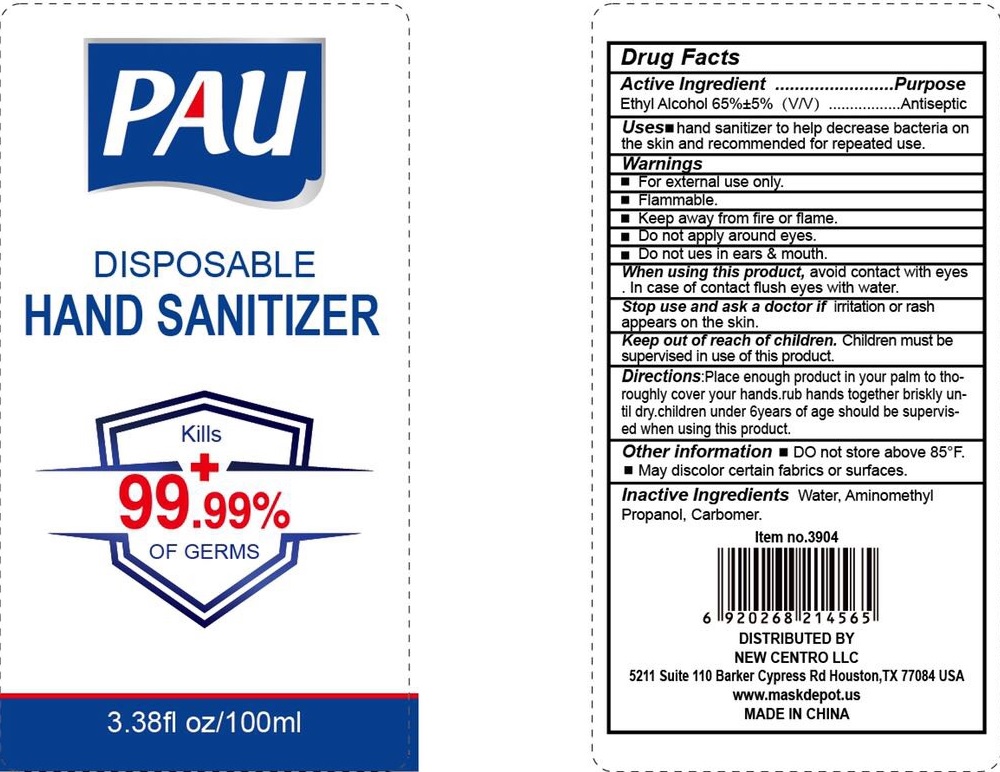 DRUG LABEL: PAU Disposable Hand Sanitizer
NDC: 75255-004 | Form: SOLUTION
Manufacturer: Guangzhou Baoli Cosmetics Co., Ltd.
Category: otc | Type: HUMAN OTC DRUG LABEL
Date: 20200514

ACTIVE INGREDIENTS: ALCOHOL 65 mL/100 mL
INACTIVE INGREDIENTS: water; AMINOMETHYLPROPANOL; CARBOMER 934

Active ingredient

Ethyl Alcohol 65%±5% (V/V)

Purpose

Antiseptic

Use

hand sanitizer to help decrease bacteria on the skin and recommended for repeated use.

KEEP OUT OF REACH OF CHILDREN

Children must be supervised in use of this product.

Warnings:

- For external use only.
- Flammable.
- Keep away from fire or flame.
- Do not apply around eyes.
- Do not use in ears and mouth.

When using this product, Avoid contact with eyes. In case of contact flush eyes with water.

Stop use and ask a doctor if irritation or rash appears on the skin.

DOSAGE AND ADMINISTRATION

Place enough product in your palm to thoroughly cover your hands rub together briskly until dry.

Children under 6 years of age should be supervised when using this product.

Other Information:

- Do not store above 85℉.
- May discolor certain fabrics or surfaces.

Inactive ingredients

Water, Aminomethyul Propanol, Carbomer.